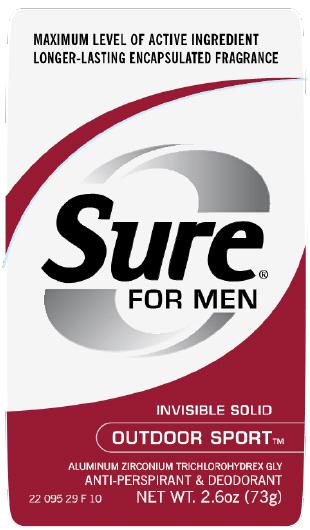 DRUG LABEL: Sure for Men Invisible Solid Antiperspirant
NDC: 41595-5522 | Form: STICK
Manufacturer: Idelle Labs, Ltd
Category: otc | Type: HUMAN OTC DRUG LABEL
Date: 20110926

ACTIVE INGREDIENTS: ALUMINUM ZIRCONIUM TRICHLOROHYDREX GLY 20 g/100 g
INACTIVE INGREDIENTS: CYCLOMETHICONE 5; STEARYL ALCOHOL; DIMETHICONE; PETROLATUM; PPG-14 BUTYL ETHER

; HYDROGENATED CASTOR OIL; TALC; STARCH, CORN; MANNITOL; MINERAL OIL; DOCOSANOL

Sure for Men Invisible Solid Antiperspirant Outdoor Sport

SURE FOR MEN
INVISIBLE SOLID
OUTDOOR SPORT
ALUMINUM ZIRCONIUM TRICHLOROHYDREX GLY
ANTI-PERSPIRANT & DEODORANT

Active Ingredient

Aluminum Zirconium Trichlorohydrex GLY 20% (anhydrous)

Purpose

Antiperspirant

Use

Reduces underarm wetness

Warnings

For external use only.

Do not use

on broken skin

Ask a doctor

before use if you have kidney disease

Stop use

if rash or irritation occurs

Keep out of reach of children.

If swallowed, get medical help or contact a Poison Control Center right away.

Directions

Apply to underarms only

Inactive Ingredients

Cyclopentasiloxane, Stearyl Alcohol, Dimethicone, Petrolatum, PPG-14 Butyl Ether, Hydrogenated Castor Oil, Talc, Fragrance, Zea Mays (Corn) Starch, Mannitol, Mineral Oil, Behenyl Alcohol

Questions?

www.sureap.com
1-800-944-4477

label